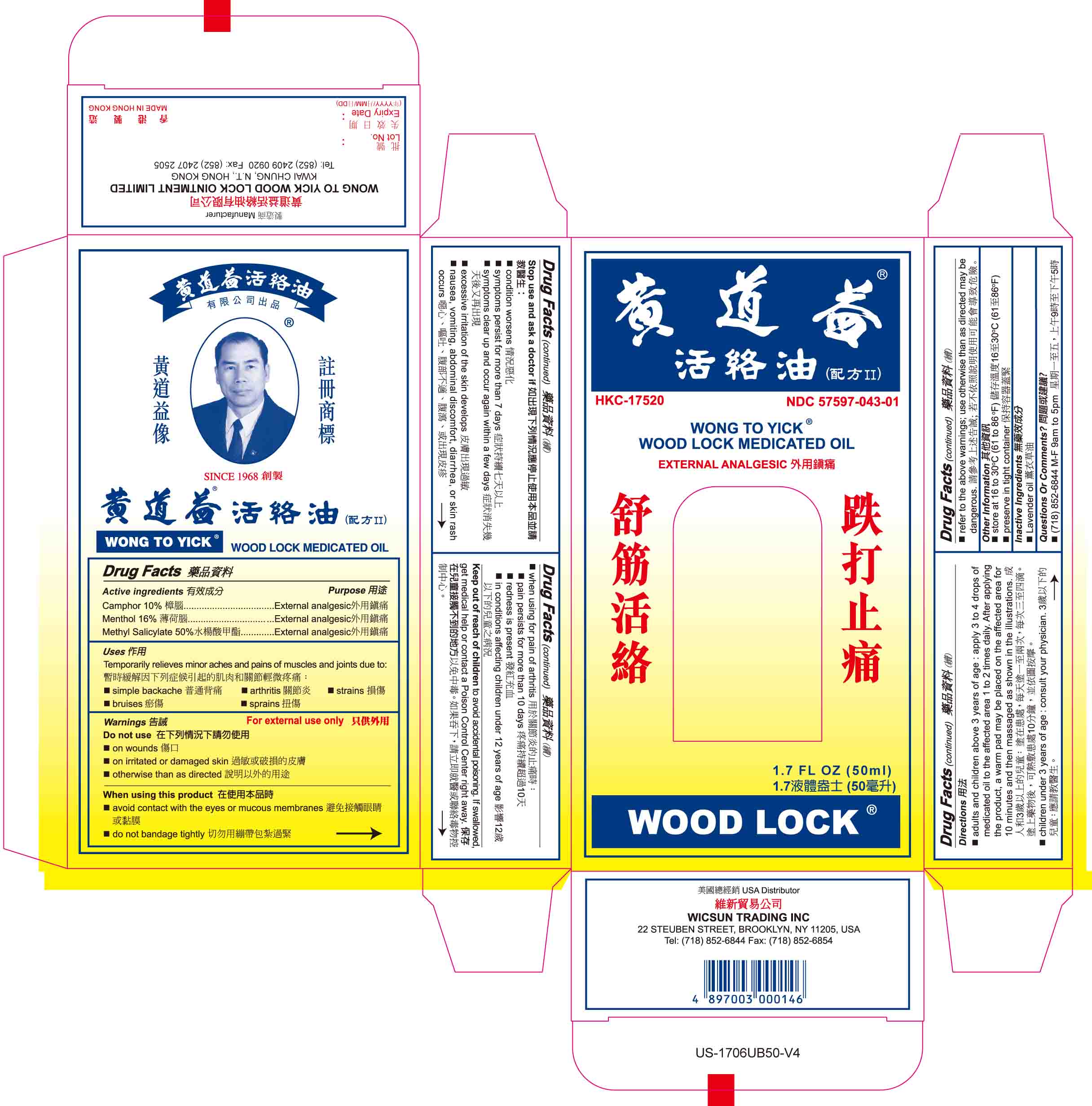 DRUG LABEL: Wong To Yick
NDC: 57597-043 | Form: OIL
Manufacturer: Wong To Yick Wood Lock Ointment Ltd
Category: otc | Type: HUMAN OTC DRUG LABEL
Date: 20241017

ACTIVE INGREDIENTS: CAMPHOR (SYNTHETIC) 1 mg/10 mL; MENTHOL 1.6 mg/10 mL; METHYL SALICYLATE 5 mg/10 mL
INACTIVE INGREDIENTS: LAVENDER OIL

WcsnWTYextrnlanglscOil

Active Ingredients

Camphor 10%
Menthol 16%
Methyl Salicylate 50%

Purpose

External Analgesic

Uses

Temporarily relieves minor aches and pains of muscles and joints due to :

- simple backache
- arthritis
- strains
- bruises
- sprains

Warnings

Do not use

- on wounds
- on irritated or damaged skin
- otherwise than as directed

When using this product

- avoid contact with the eyes or mucous membrannes
- do not bandage tightly

Stop use and ask a doctor if

- condition worsens,
- symptoms persist for more than 7 days
- symptoms clear up and occur again within a few days
- excessive irritation of the skin develops
- nausea, vomiting, abdominal discomfort, diarrhea, or skin rash occurs

when using for pain of arthritis

- pain persists for more than 10 days
- redness is present
- in conditions affecting children under 12 years of age

Keep out of reach of children

to avoid accidental poisoning. If swallowed, get medical help or contact Poison Control Center right away

Directions

- adults and children above 3 years of age: apply 3 to 4 drops of medicated oil to the affected area 1 to 2 times daily. After applying the product, a warm pad may be placed on the affected area for 10 minutes and then massaged as shown in the illustrations.
- children under 3 years of age: consult your physician.
- refer to the above warnings; use otherwise than as directed may be dangerous.

Other Information

- store at 16 to 30°C (61 to 86°F)
- preserve in tight container

Inactive Ingredients

Lavender Oil